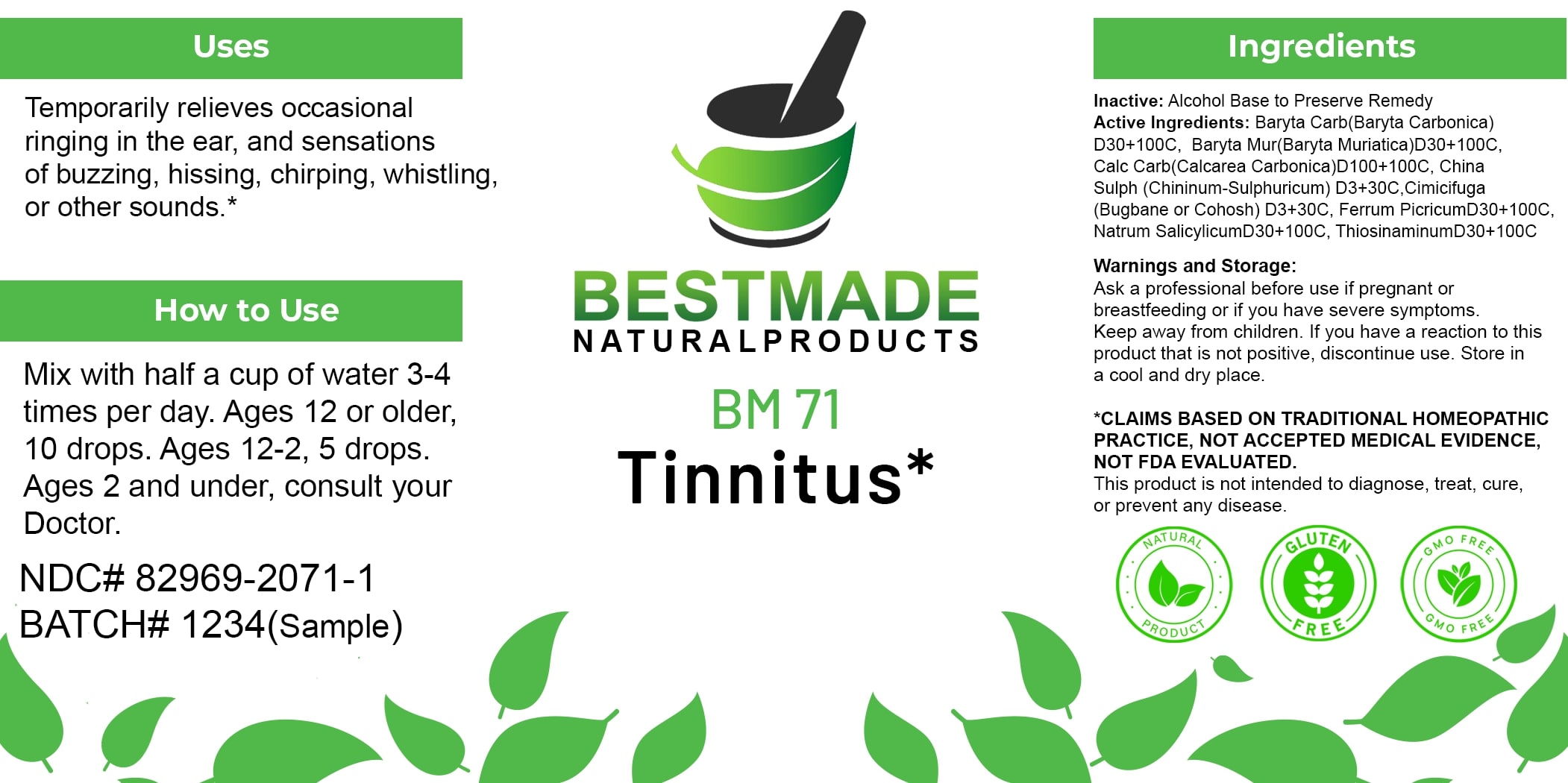 DRUG LABEL: Bestmade Natural Products BM71
NDC: 82969-2071 | Form: LIQUID
Manufacturer: Bestmade Natural Products
Category: homeopathic | Type: HUMAN OTC DRUG LABEL
Date: 20250130

ACTIVE INGREDIENTS: SODIUM SALICYLATE 30 [hp_C]/30 [hp_C]; FERRIC PICRATE 30 [hp_C]/30 [hp_C]; OYSTER SHELL CALCIUM CARBONATE, CRUDE 30 [hp_C]/30 [hp_C]; BLACK COHOSH 30 [hp_C]/30 [hp_C]; BARIUM CARBONATE 30 [hp_C]/30 [hp_C]; QUININE SULFATE 30 [hp_C]/30 [hp_C]; BARIUM CHLORIDE DIHYDRATE 30 [hp_C]/30 [hp_C]; ALLYLTHIOUREA 30 [hp_C]/30 [hp_C]
INACTIVE INGREDIENTS: ALCOHOL 30 [hp_C]/30 [hp_C]

BM71

DOSAGE AND ADMINISTRATION

How to Use

Mix with half a cup of water 3-4 times per day. Ages 12 or older, 10 drops. Ages 12-2, 5 drops. Ages 2 and under, consult your Doctor.

INACTIVE INGREDIENT

Ingredients

Inactive: Alcohol Base to Preserve Remedy

ACTIVE INGREDIENT

Active Ingredients: Baryta Carb(Baryta Carbonica) D30+100C, Baryta Mur(Baryta Muriatica)D30+100C, Calc Carb(Calcarea Carbonica)D100+100C, China Sulph (Chininum-Sulphuricum) D3+30C, Cimicifuga (Bugbane or Cohosh) D3+30C, Ferrum PicricumD30+100C, Natrum SalicylicumD30+100C, ThiosinaminumD30+100C

Uses

Temporarily relieves occasional ringing in the ear, and sensations of buzzing, hissing, chirping, whistling, or other sounds.*

*CLAIMS BASED ON TRADITIONAL HOMEOPATHIC PRACTICE, NOT ACCEPTED MEDICAL EVIDENCE, NOT FDA EVALUATED.

This product is not intended to diagnose, treat, cure, or prevent any disease.

KEEP OUT OF REACH OF CHILDREN

Warnings and Storage:

Ask a professional before use if pregnant or breastfeeding or if you have severe symptoms. Keep away from children. If you have a reaction to this product that is not positive, discontinue use. Store in a cool and dry place.

Uses

Temporarily relieves occasional ringing in the ear, and sensations of buzzing, hissing, chirping, whistling, or other sounds.*

*CLAIMS BASED ON TRADITIONAL HOMEOPATHIC PRACTICE, NOT ACCEPTED MEDICAL EVIDENCE, NOT FDA EVALUATED.

This product is not intended to diagnose, treat, cure, or prevent any disease.

Warnings and Storage:

Ask a professional before use if pregnant or breastfeeding or if you have severe symptoms. Keep away from children. If you have a reaction to this product that is not positive, discontinue use. Store in a cool and dry place.

*CLAIMS BASED ON TRADITIONAL HOMEOPATHIC PRACTICE, NOT ACCEPTED MEDICAL EVIDENCE, NOT FDA EVALUATED.

This product is not intended to diagnose, treat, cure, or prevent any disease.

Entire package label